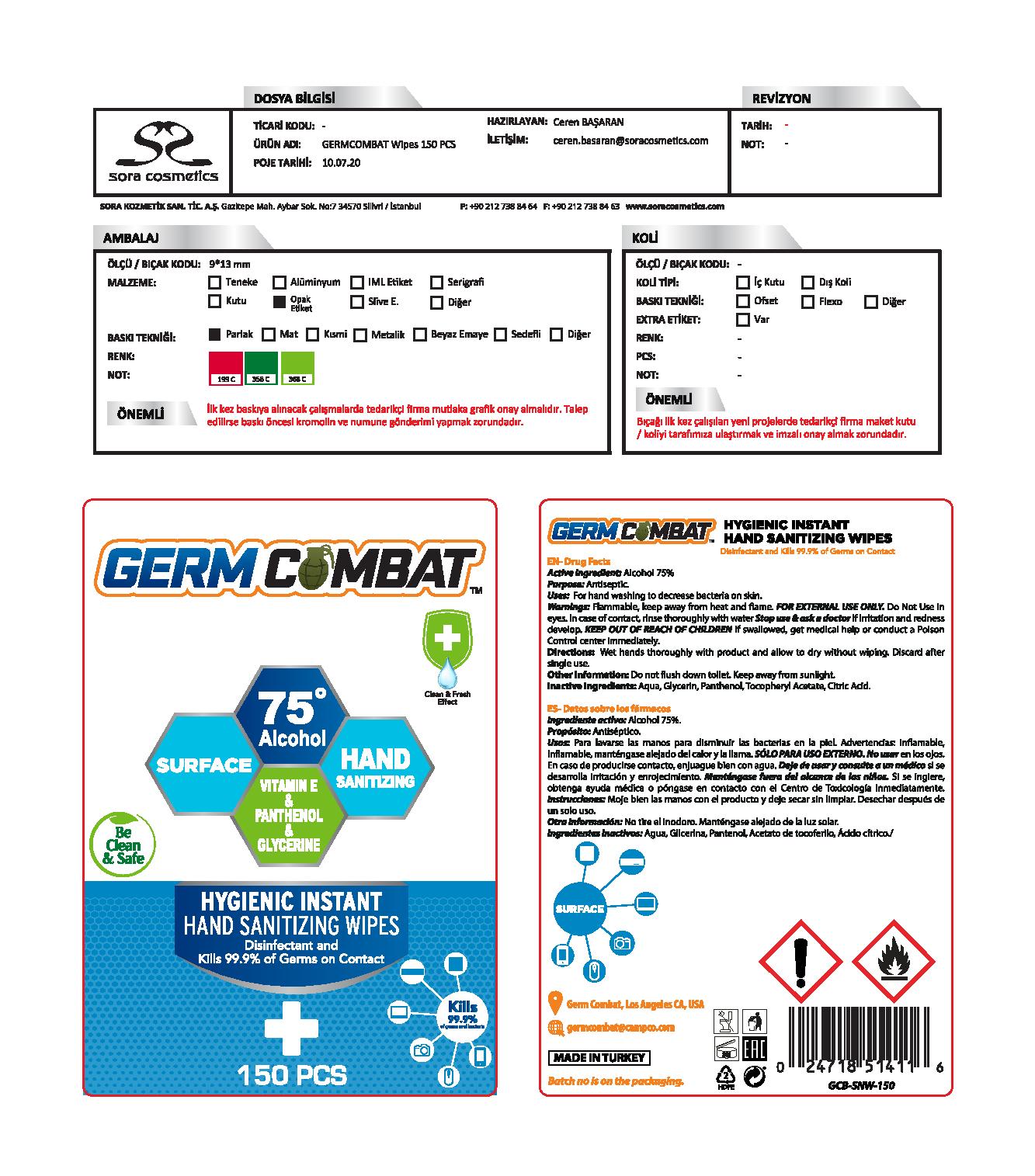 DRUG LABEL: Germ Combat
NDC: 77462-014 | Form: CLOTH
Manufacturer: SORA KOZMETIK SANAYI TICARET ANONIM SIRKETI
Category: otc | Type: HUMAN OTC DRUG LABEL
Date: 20200911

ACTIVE INGREDIENTS: ALCOHOL 112.5 mL/150 mL
INACTIVE INGREDIENTS: .ALPHA.-TOCOPHEROL ACETATE; GLYCERIN; PANTHENOL; WATER; CITRIC ACID MONOHYDRATE

Germ Combat Sanitizing Wipe

Active Ingredient

Alcohol 75%

Purpose

Antiseptic

Uses

For hand washing to decrease bacteria on skin.

Warnings

Flammable: Keep away from heat or flame.

For External Use Only

Do not use in eyes. In case of contact rinse thoroughly with water.

Stop use and ask a doctor if irritation and redness develops.

Keep out of reach of children. If swallowed, get medical help or contact a poison control center immediately.

Directions

Wet hands thoroughly with product and allow to dry without wiping. Discard after single use.

Other Information

Do not flush down toilet. Keep away from sunlight.

Inactive Ingredients

Aqua, Glycerin, Panthenol, Tocopheryl Acetate, Citric Acid